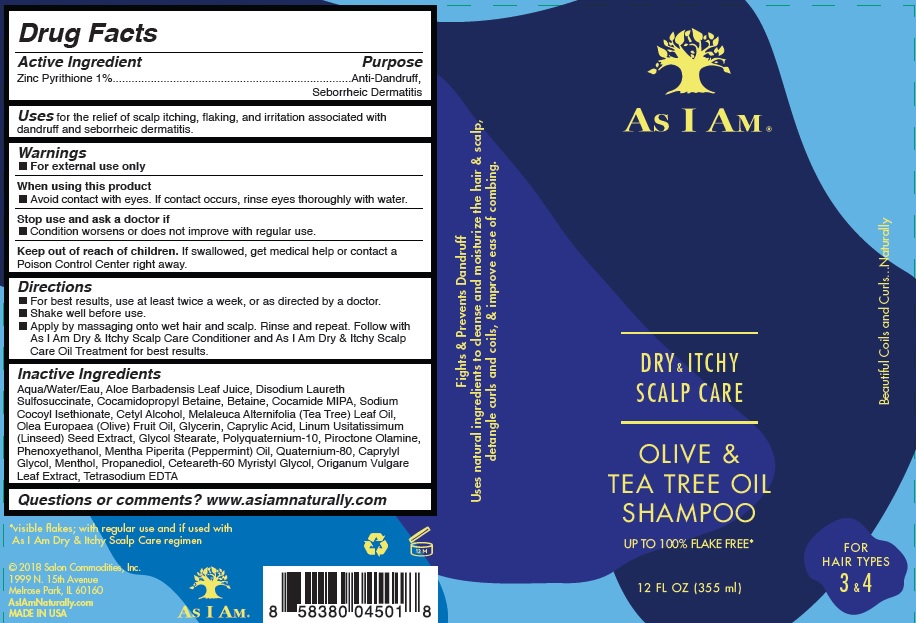 DRUG LABEL: As I Am
NDC: 72474-100 | Form: SHAMPOO
Manufacturer: Salon Commodities, Inc.
Category: otc | Type: HUMAN OTC DRUG LABEL
Date: 20241009

ACTIVE INGREDIENTS: PYRITHIONE ZINC 10 mg/1 mL
INACTIVE INGREDIENTS: COCAMIDOPROPYL BETAINE; BETAINE; DISODIUM LAURETH SULFOSUCCINATE; COCO MONOISOPROPANOLAMIDE; CETYL ALCOHOL; 2-(CYCLOHEXYLAMINO)ETHANESULFONIC ACID; CAPRYLYL GLYCOL; MENTHOL; CETEARETH-60 MYRISTYL GLYCOL; EDETATE SODIUM; TEA TREE OIL; OLIVE OIL; GLYCERIN; CAPRYLIC ACID; PHENOXYETHANOL; WATER; SODIUM COCOYL ISETHIONATE; LINSEED OIL; GLYCOL STEARATE; POLYQUATERNIUM-10 (125 MPA.S AT 2%); PIROCTONE OLAMINE; PEPPERMINT OIL; ALOE VERA LEAF; PROPANEDIOL; OREGANO

As I Am - Dry & Itchy Scalp Care - Olive and Tea Tree Oil Shampoo

Active Ingredient

Zinc Pyrithione 1%

Purpose

Anti-Dandruff, Seborrheic Dermatitis

Uses

For the relief of scalp itching, flaking, and irritation associated with dandruff and seborrheic dermatitis.

Warnings

- For external use only.

When Using This Product

- Avoid contact with eyes. If contact occurs, rinse eyes thoroughly with water.

Stop use and ask a doctor if

- Condition worsens or does not improve with regular use.

Keep out of reach of children. If swallowed, get medical help or contact a Poison Control Center right away.

Directions

- For best results, use at least twice a week, or as directed by a doctor.
- Shake well before use.
- Apply by massaging onto wet hair and scalp. Rinse and repeat. Follow with As I Am Dry & Itchy Scalp Care Conditioner and As I Am Dry & Itchy Scalp Care Oil Treatment for best results.

Inactive Ingredient

Aqua/Water/Eau, Aloe Barbadensis Leaf Juice, Disodium Laureth

Sulfosuccinate, Cocamidopropyl Betaine, Betaine, Cocamide MIPA, Sodium

Cocoyl Isethionate, Cetyl Alcohol, Melaleuca Alternifolia (Tea Tree) Leaf Oil,

Olea Europaea (Olive) Fruit Oil, Glycerin, Caprylic Acid, Linum Usitatissimum

(Linseed) Seed Extract, Glycol Stearate, Polyquaternium-10, Piroctone Olamine,

Phenoxyethanol, Mentha Piperita (Peppermint) Oil, Quaternium-80, Caprylyl

Glycol, Menthol, Propanediol, Ceteareth-60 Myristyl Glycol, Origanum Vulgare

Leaf Extract, Tetrasodium EDTA

Questions or comments? www.asiamnaturally.com

PACKAGE LABEL

As I Am - Dry & Itchy Scalp Care - Olive and Tea Tree Oil Shampoo

12 FL OZ (355 ml)

NDC 72474-100-01